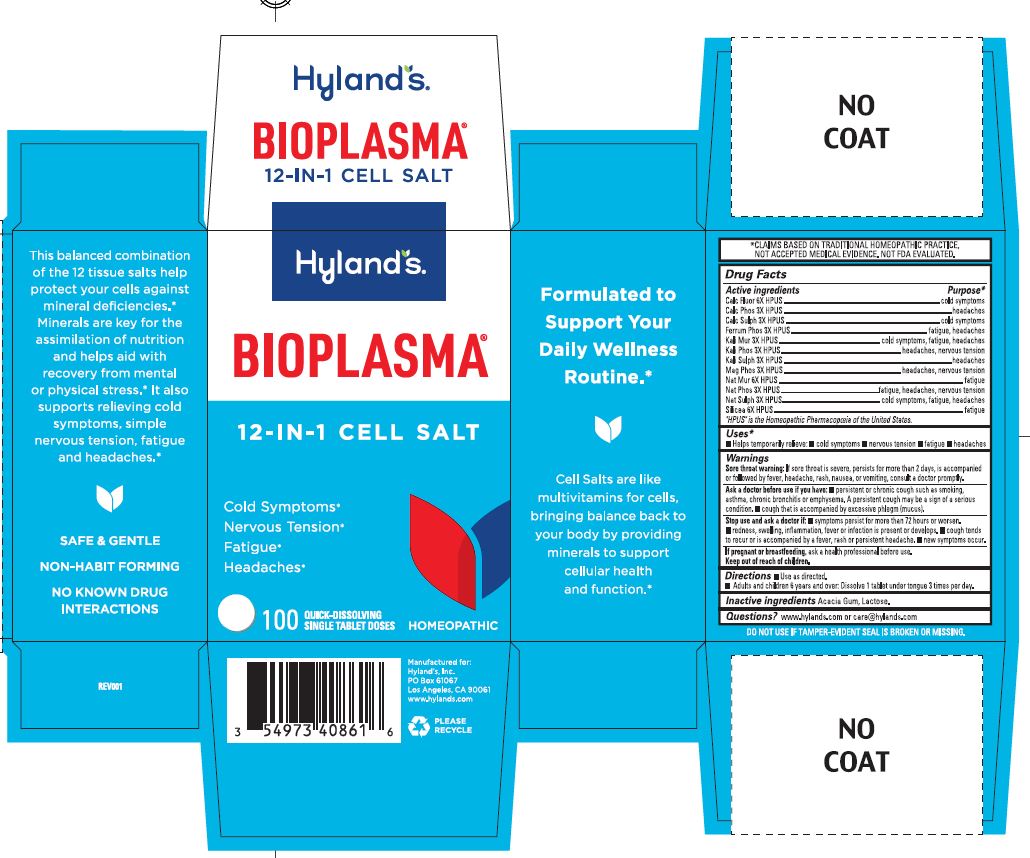 DRUG LABEL: Bioplasma
NDC: 54973-4086 | Form: TABLET, SOLUBLE
Manufacturer: Hyland's Inc.
Category: homeopathic | Type: HUMAN OTC DRUG LABEL
Date: 20250402

ACTIVE INGREDIENTS: SILICON DIOXIDE 6 [hp_X]/1 1; TRIBASIC CALCIUM PHOSPHATE 3 [hp_X]/1 1; FERROSOFERRIC PHOSPHATE 3 [hp_X]/1 1; MAGNESIUM PHOSPHATE, DIBASIC TRIHYDRATE 3 [hp_X]/1 1; SODIUM PHOSPHATE, DIBASIC, HEPTAHYDRATE 3 [hp_X]/1 1; POTASSIUM CHLORIDE 3 [hp_X]/1 1; POTASSIUM PHOSPHATE, DIBASIC 3 [hp_X]/1 1; POTASSIUM SULFATE 3 [hp_X]/1 1; SODIUM CHLORIDE 6 [hp_X]/1 1; CALCIUM SULFATE ANHYDROUS 3 [hp_X]/1 1; CALCIUM FLUORIDE 6 [hp_X]/1 1; SODIUM SULFATE 3 [hp_X]/1 1
INACTIVE INGREDIENTS: LACTOSE MONOHYDRATE; ACACIA

Cell Salt Bioplasma

Drug Facts

Active ingredients | Purpose
Calc Fluor 6X HPUS | cold symptoms
Calc Phos 3X HPUS | headaches
Calc Sulph 3X HPUS | cold symptoms
Ferrum Phos 3X HPUS | fatigue, headaches
Kali Mur 3X HPUS | cold symptoms, fatigue, headaches
Kali Phos 3X HPUS | headaches, nervous tension
Kali Sulph 3X HPUS | headaches
Mag Phos 3X HPUS | headaches, nervous tension
Nat Mur 6X HPUS | fatigue
Nat Phos 3X HPUS | fatigue, headaches, nervous tension
Nat Sulph 3X HPUS | cold symptoms, fatigue, headaches
Silicea 6X HPUS | fatigue

"HPUS" is the Homeopathic Pharmacopoeia of the United States.

Uses

■ Temporarily relieves: ■ cold symptoms ■ nervous tension ■ fatigue ■ headaches

Warnings

Sore throat warning

If sore throat is severe, persists for more than 2 days, is accompanied or followed by fever, headache, rash, nausea, or vomiting, consult a doctor promptly.

Ask a doctor before use if you have

■ persistent or chronic cough such as smoking, asthma, chronic bronchitis or emphysema. A persistent cough may be a sign of a serious condition. ■ cough that is accompanied by excessive phlegm (mucus).

Stop use and ask a doctor if

■ symptoms persist for more than 72 hours or worsen. ■ redness, swelling, inflammation, fever or infection is present or develops.

■ cough tends to recur or is accompanied by a fever, rash or persistent headache. ■ new symptoms occur.

If pregnant or breastfeeding

Ask a health professional before use.

Directions

■ Use as directed.
■ Adults and children 6 years and over: Dissolve 1 tablet under tongue 3 times per day.

Inactive ingredients

Acacia Gum, Lactose.

Questions?

www.hylands.com or care@hylands.com

Purpose

Cold Symptoms
Nervous Tension
Fatigue
Headaches

PRINCIPAL DISPLAY PANEL

Hyland's

BIOPLASMA®

12 - IN - 1 CELL SALT

Cold Symptoms*

Nervous Tension*

Fatigue*

Headaches*

100

QUICK-DISSOLVING

SINGLE TABLET DOSES

HOMEOPATHIC